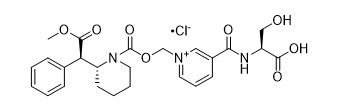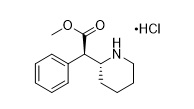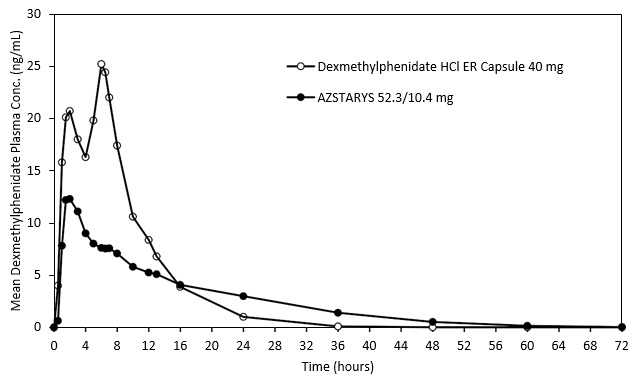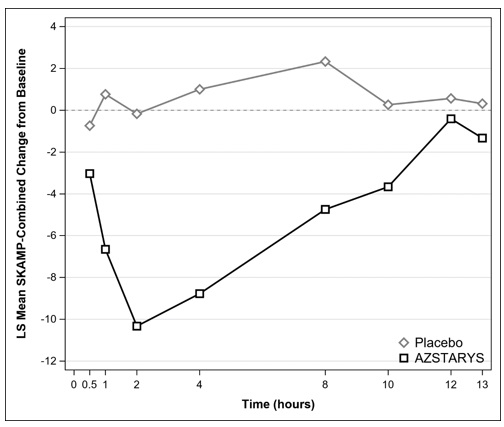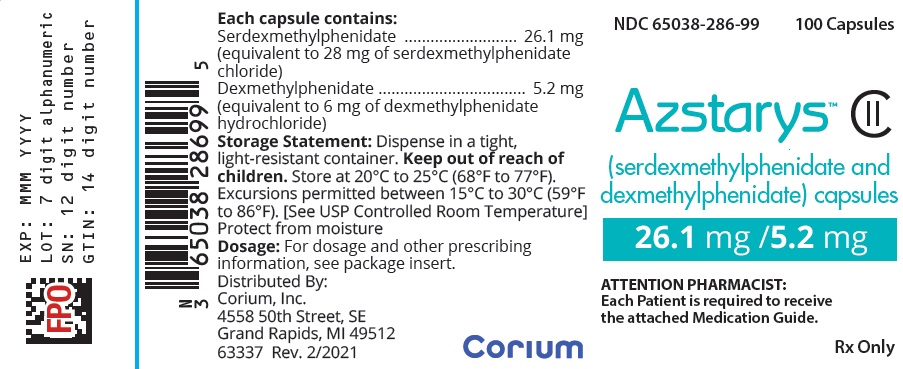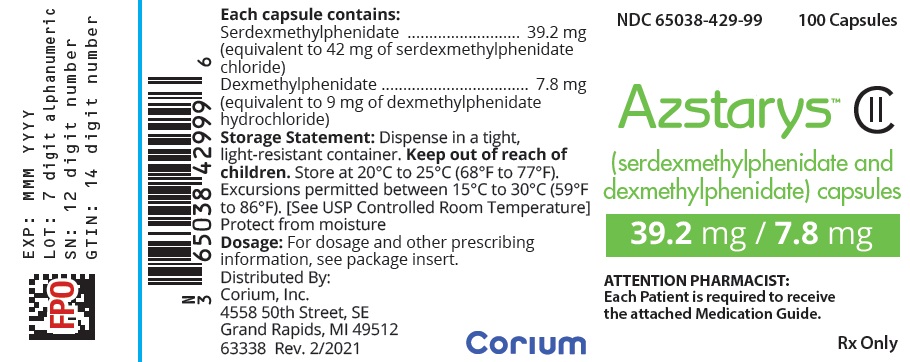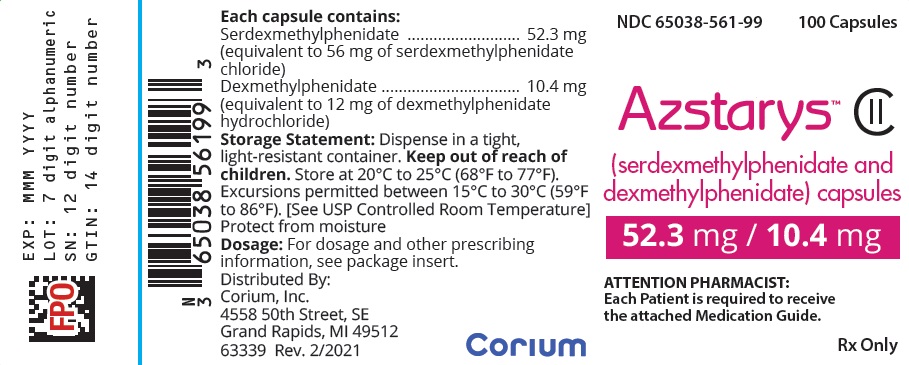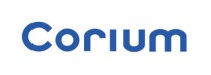 DRUG LABEL: AZSTARYS
NDC: 65038-286 | Form: CAPSULE
Manufacturer: Corium, LLC.
Category: prescription | Type: HUMAN PRESCRIPTION DRUG LABEL
Date: 20251002
DEA Schedule: CII

ACTIVE INGREDIENTS: SERDEXMETHYLPHENIDATE CHLORIDE 26.1 mg/1 1; DEXMETHYLPHENIDATE HYDROCHLORIDE 5.2 mg/1 1
INACTIVE INGREDIENTS: MICROCRYSTALLINE CELLULOSE 27.35 mg/1 1; CROSPOVIDONE 3.34 mg/1 1; MAGNESIUM STEARATE 0.68 mg/1 1; TALC 0.67 mg/1 1; SILICON DIOXIDE 0.67 mg/1 1; HYPROMELLOSE, UNSPECIFIED; FERROSOFERRIC OXIDE; FD&C BLUE NO. 1; TITANIUM DIOXIDE

HIGHLIGHTS OF PRESCRIBING INFORMATION

These highlights do not include all the information needed to use AZSTARYS safely and effectively. See full prescribing information for AZSTARYS.
AZSTARYS® (serdexmethylphenidate and dexmethylphenidate) capsules, for oral use, CII
Initial U.S. Approval: 2021

WARNING: ABUSE, MISUSE, AND ADDICTION

See full prescribing information for complete boxed warning.

AZSTARYS has a high potential for abuse and misuse, which can lead to the development of a substance use disorder, including addiction. Misuse and abuse of CNS stimulants, including AZSTARYS, can result in overdose and death (5.1, 9.2, 10):

- Before prescribing AZSTARYS, assess each patient’s risk for abuse, misuse, and addiction.
- Educate patients and their families about these risks, proper storage of the drug, and proper disposal of any unused drug.
- Throughout treatment, reassess each patient’s risk and frequently monitor for signs and symptoms of abuse, misuse, and addiction.

RECENT MAJOR CHANGES

Indications and Usage (1) 09/2025

Warnings and Precautions (5.7) 09/2025

1 INDICATIONS AND USAGE

AZSTARYS is a central nervous system (CNS) stimulant indicated for the treatment of Attention Deficit Hyperactivity Disorder (ADHD) in patients 6 years of age and older. (1)

Limitations of Use

The use of AZSTARYS is not recommended in pediatric patients younger than 6 years of age because they had higher plasma exposure and a higher incidence of adverse reactions (e.g., weight loss) than patients 6 years and older at the same dosage (5.7, 8.4).

2 DOSAGE AND ADMINISTRATION

- Pediatric Patients 6 to 12 years: Recommended starting dosage is 39.2 mg/7.8 mg orally once daily in the morning. Dosage may be increased to 52.3 mg/10.4 mg daily or decreased to 26.1 mg/5.2 mg daily after one week. Maximum recommended dosage is 52.3 mg/10.4 mg once daily. (2.2)
- Adults and Pediatric Patients 13 to 17 years: Recommended starting dosage is 39.2 mg/7.8 mg orally once daily in the morning. Increase the dosage after one week to 52.3 mg/10.4 mg once daily depending on response and tolerability. (2.2)
- Administer with or without food. (2.3)
- Swallow capsules whole or open and sprinkle onto applesauce or add to water. (2.3)
- To avoid substitution errors and overdosage, do not substitute for other methylphenidate products on a milligram-per-milligram basis. (2.4)

3 DOSAGE FORMS AND STRENGTHS

- Capsules (serdexmethylphenidate/dexmethylphenidate): 26.1 mg/5.2 mg, 39.2 mg/7.8 mg, 52.3 mg/10.4 mg. (3)

4 CONTRAINDICATIONS

- Known hypersensitivity to serdexmethylphenidate, methylphenidate, or product components. (4)
- Concurrent treatment with a monoamine oxidase inhibitor (MAOI), or use of an MAOI within the preceding 14 days. (4)

5 WARNINGS AND PRECAUTIONS

- Risks to Patients with Serious Cardiac Disease: Avoid use in patients with known structural cardiac abnormalities, cardiomyopathy, serious cardiac arrhythmias, coronary artery disease, or other serious cardiac disease. (5.2)
- Increased Blood Pressure and Heart Rate: Monitor blood pressure and pulse. (5.3)
- Psychiatric Adverse Reactions: Prior to initiating AZSTARYS, screen patients for risk factors for developing a manic episode. If new psychotic or manic symptoms occur, consider discontinuing AZSTARYS. (5.4)
- Priapism: If abnormally sustained or frequent and painful erections occur, patients should seek immediate medical attention. (5.5)
- Peripheral Vasculopathy, including Raynaud's Phenomenon: Careful observation for digital changes is necessary during AZSTARYS treatment with ADHD stimulants. Further clinical evaluation (e.g., rheumatology referral) may be appropriate for patients who develop signs or symptoms of peripheral vasculopathy. (5.6)
- Long-Term Suppression of Growth in Pediatric Patients: Monitor height and weight at appropriate intervals in pediatric patients. (5.7)
- Acute Angle Closure Glaucoma: AZSTARYS-treated patients considered at risk for acute angle closure glaucoma (e.g., patients with significant hyperopia) should be evaluated by an ophthalmologist. (5.8)
- Increased Intraocular Pressure (IOP) and Glaucoma: Prescribe AZSTARYS to patients with open-angle glaucoma or abnormally increased IOP only if the benefit of treatment is considered to outweigh the risk. Closely monitor patients with a history of increased IOP or open angle glaucoma. (5.9)
- Motor and Verbal Tics, and Worsening of Tourette’s Syndrome: Before initiating AZSTARYS, assess the family history and clinically evaluate patients for tics or Tourette’s syndrome. Regularly monitor patients for the emergence or worsening of tics or Tourette’s syndrome. Discontinue treatment if clinically appropriate. (5.10)

6 ADVERSE REACTIONS

Based on accumulated data from other methylphenidate products, the most common (>5% and twice the rate of placebo) adverse reactions are appetite decreased, insomnia, nausea, vomiting, dyspepsia, abdominal pain, weight decreased, anxiety, dizziness, irritability, affect lability, tachycardia, and blood pressure increased. (6)

To report SUSPECTED ADVERSE REACTIONS, contact Corium, LLC at 1-855-253-2407 or FDA at 1-800-FDA-1088 or www.fda.gov/medwatch.

7 DRUG INTERACTIONS

- Antihypertensive Drugs: Monitor blood pressure. Adjust dosage of antihypertensive drug as needed. (7.1)

FULL PRESCRIBING INFORMATION

WARNING: ABUSE, MISUSE, AND ADDICTION

AZSTARYS has a high potential for abuse and misuse, which can lead to the development of a substance use disorder, including addiction. Misuse and abuse of CNS stimulants, including AZSTARYS, can result in overdose and death [see Overdosage (10)], and this risk is increased with higher doses or unapproved methods of administration, such as snorting or injection.

Before prescribing AZSTARYS, assess each patient’s risk for abuse, misuse, and addiction. Educate patients and their families about these risks, proper storage of the drug, and proper disposal of any unused drug. Throughout AZSTARYS treatment, reassess each patient’s risk of abuse, misuse, and addiction and frequently monitor for signs and symptoms of abuse, misuse, and addiction [see Warnings and Precautions (5.1) and Drug Abuse and Dependence (9.2)].

1 INDICATIONS AND USAGE

AZSTARYS is indicated for the treatment of Attention Deficit Hyperactivity Disorder (ADHD) in patients 6 years of age and older.

Limitations of Use

The use of AZSTARYS is not recommended in pediatric patients younger than 6 years of age because they had higher plasma exposure and a higher incidence of adverse reactions (e.g., weight loss) than patients 6 years and older at the same dosage [see Warnings and Precautions (5.7), Use in Specific Populations (8.4)].

2 DOSAGE AND ADMINISTRATION

2.1 Pretreatment Screening

Prior to treating patients with AZSTARYS, assess:

- for the presence of cardiac disease (i.e., perform a careful history, family history of sudden death or ventricular arrhythmia, and physical exam) [see Warnings and Precautions (5.2)].
- the family history and clinically evaluate patients for motor or verbal tics or Tourette’s syndrome before initiating AZSTARYS [see Warnings and Precautions (5.10)].

2.2 Recommended Dosage

Pediatric Patients 6 to 12 years of age

- The recommended starting dosage of AZSTARYS is 39.2 mg serdexmethylphenidate/7.8 mg dexmethylphenidate once daily in the morning.
- The dosage may be increased after one week to a dosage of 52.3 mg serdexmethylphenidate/10.4 mg dexmethylphenidate per day, or decreased after one week to a dosage of 26.1 mg serdexmethylphenidate/5.2 mg dexmethylphenidate per day, depending on response and tolerability.
- Maximum recommended dosage is 52.3 mg serdexmethylphendiate/10.4 mg dexmethyphenidate once daily.

Adults and Pediatric Patients 13 to 17 years of age

- The recommended starting dosage of AZSTARYS is 39.2 mg serdexmethylphenidate/7.8 mg dexmethylphenidate once daily in the morning.
- Increase the dosage after one week to a dosage of 52.3 mg serdexmethylphenidate/10.4 mg dexmethylphenidate per day, depending on response and tolerability.
- Maximum recommended dosage is 52.3 mg serdexmethylphenidate/10.4 mg dexmethylphenidate once daily.

2.3 Administration Instructions

Administer AZSTARYS orally once daily in the morning with or without food [see Clinical Pharmacology (12.3)].

AZSTARYS capsules may be taken whole, or opened and the entire contents sprinkled into 50 mL of water or over 2 tablespoons of applesauce. Consume all the drug/food mixture immediately or within 10 minutes of mixing; do not store for future use [see Clinical Pharmacology (12.3)].

2.4 Switching from Other Methylphenidate Products

If switching from other methylphenidate products, discontinue that treatment, and titrate with AZSTARYS using the titration schedule described above.

Do not substitute AZSTARYS for other methylphenidate products on a milligram-per-milligram basis because these products have different pharmacokinetic profiles from AZSTARYS and may have different methylphenidate base composition [see Description (11), Clinical Pharmacology (12.3)].

2.5 Dosage Reduction and Discontinuation

If paradoxical aggravation of symptoms or other adverse reactions occur, reduce dosage or, if necessary, discontinue AZSTARYS. If improvement is not observed after appropriate dosage adjustment over a one-month period, discontinue AZSTARYS.

3 DOSAGE FORMS AND STRENGTHS

AZSTARYS capsules are available as:

- 26.1 mg/5.2 mg (serdexmethylphenidate/dexmethylphenidate) – blue cap/grey body, imprinted with "286" on cap and "KP415" on the body
- 39.2 mg/7.8 mg (serdexmethylphenidate/dexmethylphenidate) – dark blue cap/grey body, imprinted with "429" on cap and "KP415" on the body
- 52.3 mg/10.4 mg (serdexmethylphenidate/dexmethylphenidate) – orange cap/grey body, imprinted with "5612" on cap and "KP415" on the body

4 CONTRAINDICATIONS

AZSTARYS is contraindicated in patients:

- with known hypersensitivity to serdexmethylphenidate, methylphenidate, or other components of AZSTARYS. Bronchospasm, rash, and pruritus have been reported in patients who received AZSTARYS. Hypersensitivity reactions such as angioedema and anaphylactic reactions have been reported in patients treated with other methylphenidate products [see Adverse Reactions (6.2)].
- receiving concomitant treatment with monoamine oxidase inhibitors (MAOIs), or within 14 days following discontinuation of treatment with an MAOI, because of the risk of hypertensive crisis [see Drug Interactions (7.1)].

5 WARNINGS AND PRECAUTIONS

5.1 Abuse, Misuse, and Addiction

AZSTARYS has a high potential for abuse and misuse. The use of AZSTARYS exposes individuals to the risks of abuse and misuse, which can lead to the development of a substance use disorder, including addiction. AZSTARYS can be diverted for non-medical use into illicit channels or distribution [see Drug Abuse and Dependence (9.2)]. Misuse and abuse of CNS stimulants, including AZSTARYS, can result in overdose and death [see Overdosage (10)], and this risk is increased with higher doses or unapproved methods of administration, such as snorting or injection.

Before prescribing AZSTARYS, assess each patient’s risk for abuse, misuse, and addiction. Educate patients and their families about these risks and proper disposal of any unused drug. Advise patients to store AZSTARYS in a safe place, preferably locked, and instruct patients to not give AZSTARYS to anyone else. Throughout AZSTARYS treatment, reassess each patient’s risk of abuse, misuse, and addiction and frequently monitor for signs and symptoms of abuse, misuse, and addiction.

5.2 Risks to Patients with Serious Cardiac Disease

Sudden death has been reported in patients with structural cardiac abnormalities or other serious cardiac disease who were treated with CNS stimulants at the recommended ADHD dosage.

Avoid AZSTARYS use in patients with known structural cardiac abnormalities, cardiomyopathy, serious cardiac arrhythmia, coronary artery disease, or other serious cardiac disease.

5.3 Increased Blood Pressure and Heart Rate

CNS stimulants cause an increase in blood pressure (mean increase approximately 2 to 4 mmHg) and heart rate (mean increase approximately 3 to 6 beats per minute). Some patients may have larger increases.

Monitor all AZSTARYS-treated patients for hypertension and tachycardia.

5.4 Psychiatric Adverse Reactions

Exacerbation of Pre-Existing Psychosis

CNS stimulants may exacerbate symptoms of behavior disturbance and thought disorder in patients with a pre-existing psychotic disorder.

Induction of a Manic Episode in Patients with Bipolar Disorder

CNS stimulants may induce a manic or mixed mood episode in patients. Prior to initiating AZSTARYS treatment, screen patients for risk factors for developing a manic episode (e.g., comorbid or history of depressive symptoms or a family history of suicide, bipolar disorder, or depression).

New Psychotic or Manic Symptoms

CNS stimulants, at the recommended dosage, may cause psychotic or manic symptoms (e.g., hallucinations, delusional thinking, or mania) in patients without a prior history of psychotic illness or mania. In a pooled analysis of multiple short-term, placebo-controlled studies of CNS stimulants, psychotic or manic symptoms occurred in approximately 0.1% of CNS stimulant-treated patients, compared to 0% of placebo-treated patients. If such symptoms occur, consider discontinuing AZSTARYS.

5.5 Priapism

Prolonged and painful erections, sometimes requiring surgical intervention, have been reported with methylphenidate use, in both adult and pediatric male patients. Although priapism was not reported with methylphenidate initiation, it developed after some time on methylphenidate, often subsequent to an increase in dosage. Priapism also occurred during methylphenidate withdrawal (drug holidays or during discontinuation).

AZSTARYS-treated patients who develop abnormally sustained or frequent and painful erections should seek immediate medical attention.

5.6 Peripheral Vasculopathy, including Raynaud's Phenomenon

CNS stimulants used to treat ADHD, including AZSTARYS, are associated with peripheral vasculopathy, including Raynaud's phenomenon. Signs and symptoms are usually intermittent and mild; however, sequelae have included digital ulceration and/or soft tissue breakdown. Effects of peripheral vasculopathy, including Raynaud's phenomenon, were observed in post- marketing reports and at the therapeutic dosage of CNS stimulants in all age groups throughout the course of treatment. Signs and symptoms generally improved after dosage reduction or discontinuation of the CNS stimulant.

Careful observation for digital changes is necessary during AZSTARYS treatment. Further clinical evaluation (e.g., rheumatology referral) may be appropriate for AZSTARYS-treated patients who develop signs or symptoms of peripheral vasculopathy.

5.7 Long-Term Suppression of Growth in Pediatric Patients

AZSTARYS is not approved for use and is not recommended in pediatric patients below 6 years of age [see Use in Specific Populations (8.4)].

CNS stimulants have been associated with weight loss and slowing of growth rate in pediatric patients.

In a long-term, open-label safety study with AZSTARYS conducted in pediatric patients 6 to 12 years of age with ADHD, there was a lower than expected increase in height and weight compared to pediatric patients of the same age and sex, on average [see Adverse Reactions (6.1)].

Closely monitor growth (weight and height) in AZSTARYS-treated pediatric patients. Pediatric patients who are not growing or gaining height or weight as expected may need to have their treatment interrupted.

5.8 Acute Angle Closure Glaucoma

There have been reports of angle closure glaucoma associated with methylphenidate treatment.

Although the mechanism is not clear, AZSTARYS-treated patients considered at risk for acute angle closure glaucoma (e.g., patients with significant hyperopia) should be evaluated by an ophthalmologist.

5.9 Increased Intraocular Pressure and Glaucoma

There have been reports of an elevation of intraocular pressure (IOP) associated with methylphenidate treatment [see Adverse Reactions (6.2)].

Prescribe AZSTARYS to patients with open-angle glaucoma or abnormally increased IOP only if the benefit of treatment is considered to outweigh the risk. Closely monitor AZSTARYS-treated patients with a history of abnormally increased IOP or open angle glaucoma.

5.10 Motor and Verbal Tics, and Worsening of Tourette’s Syndrome

CNS stimulants, including methylphenidate, have been associated with the onset or exacerbation of motor and verbal tics. Worsening of Tourette’s syndrome has also been reported [see Adverse Reactions (6.2)].

Before initiating AZSTARYS, assess the family history and clinically evaluate patients for tics or Tourette’s syndrome. Regularly monitor AZSTARYS-treated patients for the emergence or worsening of tics or Tourette’s syndrome, and discontinue treatment if clinically appropriate.

6 ADVERSE REACTIONS

The following are discussed in more detail in other sections of the labeling:

- Abuse, Misuse, and Addiction [see Boxed Warning, Warnings and Precautions (5.1), and Drug Abuse and Dependence (9.2, 9.3)]
- Known hypersensitivity to methylphenidate or other ingredients of AZSTARYS [see Contraindications (4)]
- Hypertensive Crisis with Concomitant Use of Monoamine Oxidase Inhibitors [see Contraindications (4)]
- Risks to Patients with Serious Cardiac Disease [see Warnings and Precautions (5.2)]
- Increased Blood Pressure and Heart Rate [see Warnings and Precautions (5.3)]
- Psychiatric Adverse Reactions [see Warnings and Precautions (5.4)]
- Priapism [see Warnings and Precautions (5.5)]
- Peripheral Vasculopathy, including Raynaud's Phenomenon [see Warnings and Precautions (5.6)]
- Long-Term Suppression of Growth in Pediatric Patients [see Warnings and Precautions (5.7)]
- Acute Angle Closure Glaucoma [see Warnings and Precautions (5.8)]
- Increased Intraocular Pressure and Glaucoma [see Warnings and Precautions (5.9)]
- Motor and Verbal Tics, and Worsening of Tourette’s Syndrome [see Warnings and Precautions (5.10)]

6.1 Clinical Trials Experience

Because clinical trials are conducted under widely varying conditions, adverse reaction rates observed in the clinical trials of a drug cannot be directly compared to rates in the clinical trials of another drug and may not reflect the rates observed in clinical practice.

Adverse Reactions in Studies with Other Methylphenidate Products in Pediatric Patients and Adults with ADHD

Commonly reported (≥ 5% of the methylphenidate group and at least twice the rate of the placebo group) adverse reactions from placebo-controlled trials of methylphenidate products include: decreased appetite, decreased weight, nausea, abdominal pain, dyspepsia, vomiting, insomnia, anxiety, affect lability, irritability, dizziness, increased blood pressure, and tachycardia.

Adverse Reactions in Studies with AZSTARYS in Pediatric Patients (6 to 12 years) with ADHD

Short-Term Study

A short-term study conducted in pediatric patients 6 to 12 years of age with ADHD was comprised of a 3-week, open-label, dose optimization phase in which all patients received AZSTARYS (n=155), followed by a 1-week, double-blind, controlled phase in which patients were randomized to continue AZSTARYS (n=74) or switch to placebo (n=76). Because of the study design, the reported adverse reaction rates cannot be used to predict the rates that may be expected in clinical practice.

Long-Term Study

A long-term, open-label safety study was conducted in pediatric patients 6 to 12 years of age with ADHD who either completed the short-term study or were de novo patients. This study was comprised of a 3-week dose optimization phase for patients not recently treated with AZSTARYS followed by a 12-month treatment phase for all patients during which 238 patients received open- label AZSTARYS and had evaluable safety data. A total of 154 patients were treated for 12 months. Because of the open-label, uncontrolled design of this study, the reported adverse reaction rates cannot be assessed in terms of a causal relationship to AZSTARYS treatment.

To adjust for normal growth, z-scores were derived (measured in standard deviations [SD]); z- scores normalize for the natural growth of children and adolescents by comparisons to age- and sex-matched population standards. A z-score change less than 0.5 SD is considered not clinically significant.

In this study, the mean increase in weight from baseline to Month 12 was 3.4 kg among study completers. The mean change in z-score from baseline to Month 12 was -0.20, indicating a lower than expected increase in body weight compared to children of the same age and sex, on average. Most of the weight z-score decline occurred in the first 4 months of treatment.

The mean increase in height from baseline to Month 12 was 4.9 cm among completers. Using the same z-score analysis for height, the mean change in z-score from baseline to Month 12 was - 0.21, indicating a lower than expected increase in height compared to pediatric patients of the same age and sex, on average.

6.2 Postmarketing Experience

The following adverse reactions have been identified during post approval use of methylphenidate products. Because these reactions are reported voluntarily from a population of uncertain size, it is not possible to reliably estimate their frequency or establish a causal relationship to drug exposure. These adverse reactions are as follows:

Blood and Lymphatic System Disorders: pancytopenia, thrombocytopenia, thrombocytopenic purpura

Cardiac Disorders: angina pectoris, bradycardia, extrasystole, supraventricular tachycardia, ventricular extrasystole, palpitations, increased heart rate

Eye Disorders: diplopia, increased intraocular pressure, mydriasis, visual impairment, blurred vision

General Disorders: chest pain, chest discomfort, hyperpyrexia

Gastrointestinal Disorders: dry mouth

Hepatobiliary disorders: hepatocellular injury, acute hepatic failure

Immune System Disorders: hypersensitivity reactions such as angioedema, anaphylactic reactions, auricular swelling, bullous conditions, exfoliative conditions, urticarias, pruritus NEC, rashes, eruptions, and exanthemas NEC

Investigations: alkaline phosphatase increased, bilirubin increased, hepatic enzyme increased, platelet count decreased, white blood cell count abnormal

Musculoskeletal, Connective Tissue and Bone Disorders: arthralgia, myalgia, muscle twitching, rhabdomyolysis, muscle cramps

Nervous System: convulsion, grand mal convulsion, dyskinesia, serotonin syndrome in combination with serotonergic drugs, nervousness, headache, tremor, drowsiness, vertigo, motor and verbal tics

Psychiatric Disorders: disorientation, libido changes, hallucination, hallucination auditory, hallucination visual, logorrhea, mania, restlessness, agitation

Skin and Subcutaneous Tissue Disorders: alopecia, erythema, hyperhidrosis

Urogenital System: priapism

Vascular Disorders: Raynaud's phenomenon

7 DRUG INTERACTIONS

7.1 Clinically Important Interactions with AZSTARYS

Table 1 presents clinically important drug interactions with AZSTARYS.

Table 1: Clinically Important Drug Interactions with AZSTARYS
Monoamine Oxidase Inhibitors (MAOIs)
Clinical Impact | Concomitant use of MAOIs and CNS stimulants, including AZSTARYS, can cause hypertensive crisis. Potential outcomes include death, stroke, myocardial infarction, aortic dissection, ophthalmological complications, eclampsia, pulmonary edema, and renal failure [see Contraindications (4)].
Intervention | Do not administer AZSTARYS concomitantly with MAOIs or within 14 days after discontinuing MAOI treatment [see Contraindications (4)]
Antihypertensive Drugs
Clinical Impact | AZSTARYS may decrease the effectiveness of drugs used to treat hypertension [see Warnings and Precautions (5.3)].
Intervention | Monitor blood pressure and adjust the dosage of the antihypertensive drug, as needed.
Halogenated Anesthetics
Clinical Impact | Concomitant use of halogenated anesthetics and AZSTARYS may increase the risk of sudden blood pressure and heart rate increase during surgery.
Intervention | Avoid use of AZSTARYS in patients being treated with anesthetics on the day of surgery.
Risperidone
Clinical Impact | Combined use of methylphenidate with risperidone when there is a change, whether an increase or decrease, in dosage of either or both medications, may increase the risk of extrapyramidal symptoms (EPS).
Intervention | Monitor for signs of EPS.

8 USE IN SPECIFIC POPULATIONS

8.1 Pregnancy

Pregnancy Exposure Registry

There is a pregnancy exposure registry that monitors pregnancy outcomes in women exposed to ADHD medications, including AZSTARYS, during pregnancy. Healthcare providers are encouraged to register patients by calling the National Pregnancy Registry for Psychostimulants at 1-866-961-2388.

Risk Summary

There are no available data on AZSTARYS use in pregnant women to evaluate for a drug- associated risk of major birth defects, miscarriage or other adverse maternal or fetal outcomes; however, AZSTARYS contains dexmethylphenidate and serdexmethylphenidate, a prodrug of dexmethylphenidate. Dexmethylphenidate is the d-threo enantiomer of racemic methylphenidate. Published studies and postmarketing reports on methylphenidate use during pregnancy have not identified a drug-associated risk of major birth defects, miscarriage or adverse maternal or fetal outcomes. There may be risks to the fetus associated with the use of CNS stimulants use during pregnancy (see Clinical Considerations). Embryo-fetal development studies in rats showed delayed fetal skeletal ossification at doses up to 3 times the maximum recommended human dose (MRHD) of 40 mg/day dexmethylphenidate hydrochloride given to adults based on plasma levels. A decrease in pup weight in males was observed in a pre- and post-natal development study with oral administration of dexmethylphenidate to rats throughout pregnancy and lactation at doses 3 times the MRHD of 40 mg/day dexmethylphenidate hydrochloride given to adults based on plasma levels (see Data).

No evidence of developmental effects were found in an embryo-fetal development study with oral administration of serdexmethylphenidate to rabbits during organogenesis at doses up to approximately 49 times the MRHD of 52 mg/day serdexmethylphenidate given to adults based on plasma levels (see Data).

The estimated background risk of major birth defects and miscarriage for the indicated population is unknown. All pregnancies have a background risk of birth defect, loss, or other adverse outcomes. In the U.S. general population, the estimated background risk of major birth defects and miscarriage in clinically recognized pregnancies is 2 to 4% and 15 to 20%, respectively.

Clinical Considerations

Fetal/Neonatal Adverse Reactions

CNS stimulants, such as AZSTARYS, can cause vasoconstriction and thereby decrease placental perfusion. No fetal and/or neonatal adverse reactions have been reported with the use of therapeutic doses of methylphenidate during pregnancy; however, premature delivery and low birth weight infants have been reported in amphetamine-dependent mothers.

Data

Animal Data

In embryo-fetal development studies conducted in rats and rabbits, dexmethylphenidate hydrochloride was administered orally at doses of up to 20 and 100 mg/kg/day, respectively, during the period of organogenesis. No evidence of malformations was found in either the rat or rabbit study; however, delayed fetal skeletal ossification was observed at the highest dose level in rats. When dexmethylphenidate hydrochloride was administered to rats throughout pregnancy and lactation at doses of up to 20 mg/kg/day, post-weaning body weight gain was decreased in male offspring at the highest dose, but no other effects on postnatal development were observed. At the highest doses tested, plasma levels [area under the curves (AUCs)] of dexmethylphenidate in pregnant rats and rabbits were approximately 3 and 1 times, respectively, those in adults dosed with 40 mg/day dexmethylphenidate hydrochloride.

Racemic methylphenidate hydrochloride has been shown to cause malformations (increased incidence of fetal spina bifida) in rabbits when given in doses of 200 mg/kg/day throughout organogenesis.

No evidence of developmental effects were found in an embryo-fetal development study with oral administration of serdexmethylphenidate in rabbits during organogenesis at doses of up to 374 mg/kg/day. At the highest dose tested, the plasma level [area under the curve (AUC)] of serdexmethylphenidate in pregnant rabbits was approximately 49 times that in adults dosed with 52 mg/day serdexmethylphenidate.

8.2 Lactation

Risk Summary

There are no available data on the presence of serdexmethylphenidate in human milk, effects on the breastfed infant, or effects on milk production. Dexmethylphenidate is the d-threo enantiomer of racemic methylphenidate. Limited published literature, based on milk sampling from seven mothers reports that methylphenidate is present in human milk, which resulted in infant doses of 0.16% to 0.7% of the maternal weight-adjusted dosage and a milk/plasma ratio ranging between 1.1 and 2.7. There are no reports of adverse effects on the breastfed infant and no effects on milk production. Long-term neurodevelopmental effects on infants from stimulant exposure are unknown. The developmental and health benefits of breastfeeding should be considered along with the mother's clinical need for AZSTARYS and any potential adverse effects on the breastfed infant from AZSTARYS or from the underlying maternal condition.

Clinical Considerations

Monitor breastfeeding infants for adverse reactions, such as agitation, anorexia, and reduced weight gain.

8.4 Pediatric Use

The safety and effectiveness of AZSTARYS have not been established in pediatric patients below the age of 6 years. In studies evaluating extended-release methylphenidate products, patients 4 to <6 years of age had higher systemic methylphenidate exposures than those observed in older pediatric patients at the same dosage. Pediatric patients 4 to <6 years of age also had a higher incidence of adverse reactions, including weight loss.

The safety and effectiveness of AZSTARYS have been established in pediatric patients ages 6 to 17 years of age for the treatment of ADHD. Use of AZSTARYS in patients 6 to 12 years of age is supported by a randomized, double-blind, placebo-controlled, parallel group trial in 155 pediatric patients with ADHD and a 12-month open-label long term safety trial in 238 patients [see Adverse Reactions (6.1), Clinical Studies (14)]. Use of AZSTARYS in pediatric patients 13 to 17 years of age is supported by additional pharmacokinetics analysis showing similar plasma concentration-time profiles of dexmethylphenidate in adolescents and adults after administration of the same dose of AZSTARYS [see Clinical Studies (14)].

Long Term Suppression of Growth

Growth should be monitored during treatment with stimulants, including AZSTARYS. Pediatric patients who are not growing or gaining weight as expected may need to have their treatment interrupted [see Warnings and Precautions (5.7) and Adverse Reactions (6.1)].

Juvenile Animal Toxicity Data

Rats treated with racemic methylphenidate early in the postnatal period through sexual maturation demonstrated a decrease in spontaneous locomotor activity in adulthood. A deficit in acquisition of a specific learning task was observed in females only. The doses at which these findings were observed are at least 3 times the MRHD of 40 mg/day dexmethylphenidate hydrochloride given to children on a mg/m^2 basis.

In a study conducted in young rats, racemic methylphenidate hydrochloride was administered orally at doses of up to 100 mg/kg/day for 9 weeks, starting early in the postnatal period (postnatal Day 7) and continuing through sexual maturity (postnatal Week 10). When these animals were tested as adults (postnatal Weeks 13 to 14), decreased spontaneous locomotor activity was observed in males and females previously treated with 50 mg/kg/day racemic methylphenidate hydrochloride [approximately 3 times the maximum recommended human dose (MRHD) of 40 mg of dexmethylphenidate hydrochloride given to children on a mg/m^2 basis] or greater, and a deficit in the acquisition of a specific learning task was seen in females exposed to the highest dose (6 times the MRHD of 40 mg of dexmethylphenidate hydrochloride given to children on a mg/m^2 basis). The no effect level for juvenile neurobehavioral development in rats was 5 mg/kg/day racemic methylphenidate hydrochloride (less than the MRHD of 40 mg of dexmethylphenidate hydrochloride given to children on a mg/m^2 basis). The clinical significance of the long-term behavioral effects observed in rats is unknown.

Serdexmethylphenidate was administered orally to juvenile rabbits at doses up to 280 mg/kg/day (approximately 50 times the MRHD of 52 mg/day serdexmethylphenidate given to children on a mg/m^2 basis), respectively, for 6 months, starting at postnatal Day 28 and continuing through sexual maturity (postnatal Day 196). No adverse findings were observed at the highest dose of serdexmethylphenidate.

8.5 Geriatric Use

Clinical trials of AZSTARYS did not include any patients aged 65 years and over.

9 DRUG ABUSE AND DEPENDENCE

9.1 Controlled Substance

AZSTARYS contains dexmethylphenidate hydrochloride, a Schedule II controlled substance, and serdexmethylphenidate, a Schedule IV controlled substance.

9.2 Abuse

AZSTARYS has a high potential for abuse and misuse which can lead to the development of a substance use disorder, including addiction [see Warnings and Precautions (5.1)]. AZSTARYS can be diverted for non-medical use into illicit channels or distribution.

Abuse is the intentional non-therapeutic use of a drug, even once, to achieve a desired psychological or physiological effect. Misuse is the intentional use, for therapeutic purposes, of a drug by an individual in a way other than prescribed by a health care provider or for whom it was not prescribed. Drug addiction is a cluster of behavioral, cognitive, and physiological phenomena that may include a strong desire to take the drug, difficulties in controlling drug use (e.g., continuing drug use despite harmful consequences, giving a higher priority to drug use than other activities and obligations), and possible tolerance or physical dependence.

Misuse and abuse of the combination of dexmethylphenidate and serdexmethylphenidate may cause increased heart rate, respiratory rate, or blood pressure; sweating; dilated pupils; hyperactivity; restlessness; insomnia; decreased appetite; loss of coordination; tremors; flushed skin; vomiting; and/or abdominal pain. Anxiety, psychosis, hostility, aggression, and suicidal or homicidal ideation have also been observed with CNS stimulants abuse and/or misuse. Misuse and abuse of CNS stimulants, including AZSTARYS, can result in overdose and death [see Overdosage (10)], and this risk is increased with higher doses or unapproved methods of administration, such as snorting or injection.

9.3 Dependence

Physical Dependence

AZSTARYS may produce physical dependence. Physical dependence is a state that develops as a result of physiological adaptation in response to repeated drug use, manifested by withdrawal signs and symptoms after abrupt discontinuation or a significant dose reduction of a drug.

Withdrawal signs and symptoms after abrupt discontinuation or dose reduction following prolonged use of CNS stimulants including AZSTARYS include dysphoric mood; depression; fatigue; vivid, unpleasant dreams; insomnia or hypersomnia; increased appetite; and psychomotor retardation or agitation.

Tolerance

AZSTARYS may produce tolerance. Tolerance is a physiological state characterized by a reduced response to a drug after repeated administration (i.e., a higher dose of a drug is required to produce the same effect that was once obtained at a lower dose).

10 OVERDOSAGE

Clinical Effects of Overdose

Overdose of CNS stimulants is characterized by the following sympathomimetic effects:

- Cardiovascular effects including tachyarrhythmias, and hypertension or hypotension. Vasospasm, myocardial infarction, or aortic dissection may precipitate sudden cardiac death. Takotsubo cardiomyopathy may develop.
- CNS effects including psychomotor agitation, confusion, and hallucinations. Serotonin syndrome, seizures, cerebral vascular accidents, and coma may occur.
- Life-threatening hyperthermia (temperatures greater than 104°F) and rhabdomyolysis may develop.

Overdose Management

Consider the possibility of multiple drug ingestion. The pharmacokinetic profile of AZSTARYS should be considered when treating patients with overdose. Because methylphenidate has a large volume of distribution and is rapidly metabolized, dialysis is not useful. Consider contacting the Poison Help line (1-800-222-1222) or a medical toxicologist for additional overdose management recommendations.

11 DESCRIPTION

AZSTARYS (serdexmethylphenidate and dexmethylphenidate) capsules contain dexmethylphenidate, a CNS stimulant, and serdexmethylphenidate, a prodrug of dexmethylphenidate.

AZSTARYS capsules are intended for oral administration and each capsule contains a fixed molar ratio of 30% dexmethylphenidate and 70% serdexmethylphenidate.

AZSTARYS contains 26.1/5.2, 39.2/7.8, or 52.3/10.4 mg of serdexmethylphenidate/ dexmethylphenidate (equivalent to 28/6, 42/9, or 56/12 mg of serdexmethylphenidate chloride/ dexmethylphenidate hydrochloride, respectively. The combined molar dose of serdexmethylphenidate and dexmethylphenidate in each dosage strength of AZSTARYS is equivalent to 20, 30, or 40 mg dexmethylphenidate hydrochloride, respectively (equivalent to 17.3, 25.9 or 34.6 mg dexmethylphenidate free base, respectively).

The chemical name of serdexmethylphenidate chloride is 3-(((1S)-1-carboxy-2-hydroxyethyl)carbamoyl)-1-((((2R)-2-(2-(1R)-methoxy-2-oxo-1-phenylethyl)piperidine-1-carbonyl)oxy)methyl)pyridinium chloride. Its molecular formula is C25H30N3O8^+•Cl^-, and its structural formula is:

Serdexmethylphenidate chloride is a white to off-white crystalline powder. Its solutions are acid to litmus. It is freely soluble in water, soluble in methanol, and slightly soluble in alcohol and acetone. Its molecular weight is 535.98 g/mol.

Dexmethylphenidate is the d-threo enantiomer of racemic d,l-methylphenidate hydrochloride. The chemical name of dexmethylphenidate hydrochloride is methyl (R)-2-phenyl-2-((R)-piperidin-2-yl)acetate hydrochloride. Its molecular formula is C14H19NO2•HCl, and its structural formula is:

Dexmethylphenidate hydrochloride is a white to off-white powder. Its solutions are acid to litmus. It is freely soluble in water and in methanol, soluble in alcohol, and slightly soluble in chloroform and in acetone. Its molecular weight is 269.77 g/mol.

Inactive ingredients: colloidal silicon dioxide, crospovidone, hypromellose, magnesium stearate, microcrystalline cellulose, and talc.

Each strength capsule also contains colorant ingredients in the capsule shell as follows:

- 26.1/5.2 mg: Black Iron Oxide, FD&C Blue No. 1, Titanium Dioxide
- 39.2/7.8 mg: Black Iron Oxide, FD&C Blue No. 1, FD&C Red No. 40, Titanium Dioxide
- 52.3/10.4 mg: Black Iron Oxide, FD&C Red No. 40, FD&C Yellow No. 6, Titanium Dioxide

12 CLINICAL PHARMACOLOGY

12.1 Mechanism of Action

Serdexmethylphenidate is a prodrug of dexmethylphenidate. Dexmethylphenidate HCl is a central nervous system (CNS) stimulant. The mode of therapeutic action in ADHD is not known.

12.2 Pharmacodynamics

Dexmethylphenidate

Dexmethylphenidate is the more pharmacologically active d-enantiomer of racemic d,l-methylphenidate. Methylphenidate blocks the reuptake of norepinephrine and dopamine into the presynaptic neuron and increase the release of these monoamines into the extraneuronal space. In vitro studies with serdexmethylphenidate showed little or no binding of the prodrug to monoaminergic reuptake transporters.

Cardiac Electrophysiology

The effect of serdexmethylphenidate on QTc interval was evaluated in a randomized, double-blind, placebo-controlled, human abuse potential study (intranasal administration) in 46 healthy subjects. At a mean concentration 40 times the Cmax for the highest dose of AZSTARYS (52.3/10.4 mg base equivalent), serdexmethylphenidate does not prolong the QT interval to any clinically relevant extent.

12.3 Pharmacokinetics

Serdexmethylphenidate is a prodrug of dexmethylphenidate. Following a single dose administration of 52.3 mg/10.4 mg AZSTARYS and 40 mg of an dexmethylphenidate hydrochloride extended-release (ER) capsule in healthy volunteers under fasted conditions:

- The mean peak plasma concentration (Cmax) of dexmethylphenidate was 14.0 ng/mL and 28.2 ng/mL, respectively;
- The mean area under concentration curve (AUC) of dexmethylphenidate was 186 hour*ng/mL and 248 hour*ng/mL, respectively.

The plasma PK profiles of dexmethylphenidate following administration of AZSTARYS or dexmethylphenidate hydrochloride extended-release (ER) capsule are presented in Figure 1.

Figure 1: Mean Dexmethylphenidate Plasma Concentration-Time Profiles After A Single Dose Administration of AZSTARYS or Dexmethylphenidate Hydrochloride Extended-Release (ER) Capsule in Healthy Adults Under Fasted Conditions

Approximate linear PK was demonstrated for dexmethylphenidate following single dose administration of AZSTARYS in the dose range of 26.1 mg/5.2 mg to 52.3 mg/10.4 mg. Steady state of dexmethylphenidate was approached after the third once-daily dose. At steady-state, dexmethylphenidate mean exposures (Cmax and AUC0-24h) were approximately 37% higher relative to a single-dose administration of AZSTARYS. No accumulation of serdexmethylphenidate was observed after once-daily administration of AZSTARYS. The mean relative exposure of serdexmethylphenidate to dexmethylphenidate based on molar concentrations for Cmax, Cmin, and AUC0-24hr was about 101%, 8.5%, and 55.7%, respectively, following multiple once-daily oral dosing under fasted conditions.

Absorption

Cross-study calculation estimated an absolute oral bioavailability for serdexmethylphenidate of less than 3%. The median time to reach Cmax of serdexmethylphenidate and dexmethylphenidate (Tmax) is about 2 hours following a single dose administration of AZSTARYS under fasted conditions. Following oral administration of serdexmethylphenidate single moiety alone, dexmethylphenidate Tmax is reached at about 8 hours post dose.

Effect of Food

No clinically meaningful differences in the exposure of dexmethylphenidate were observed when administered after an overnight fast, with a high-fat, high-caloric meal, or sprinkled onto applesauce or water. The median time to peak plasma concentration (Tmax) was lengthened from 2 to 4-4.5 hours in the presence of food.

Distribution

Plasma protein binding of serdexmethylphenidate and dexmethylphenidate is approximately 56% and 47%, respectively, at 5 µM (about 60-fold higher than the therapeutic concentrations at the highest recommended dose). The mean apparent volume of distribution for serdexmethylphenidate was about 29.3 L/kg after AZSTARYS administration. Dexmethylphenidate shows a mean volume of distribution of 2.65 L/kg after intravenous administration.

Elimination

The mean plasma terminal elimination half-life of serdexmethylphenidate and dexmethylphenidate in healthy adult subjects was about 5.7 hours and 11.7 hours, respectively, following a single dose of 52.3 mg/10.4 mg AZSTARYS. The mean apparent clearance for serdexmethylphenidate was about 3.6 L/hr/kg after AZSTARYS administration. Dexmethylphenidate was eliminated with a mean clearance of 0.40 L/hr/kg after intravenous administration.

Metabolism

Serdexmethylphenidate is a prodrug of dexmethylphenidate and is likely converted to dexmethylphenidate mainly in the lower gastrointestinal tract. Enzymes involved in the conversion process are not identified.

Dexmethylphenidate is metabolized primarily via de-esterification to d-α-phenyl-piperidine acetic acid (also known as d-ritalinic acid). Ritalinic acid has little or no pharmacological activity. There is no in vivo interconversion to the l-threo-enantiomer observed.

Excretion

After oral dosing of radiolabeled serdexmethylphenidate in humans, about 62% and 37% of the radioactivity was recovered in urine and feces, respectively. Metabolite ritalinic acid accounted for approximately 63% of the total recovered dose in urine and feces. About 0.4% and 11% of the dose was excreted as unchanged serdexmethylphenidate in the urine and feces, respectively.

After oral dosing of radiolabeled racemic methylphenidate in humans, about 90% of the radioactivity was recovered in urine. The main urinary metabolite of racemic d,l-methylphenidate was d,l-ritalinic acid, accountable for approximately 80% of the dose. Urinary excretion of unchanged methylphenidate accounted for 0.5% of an intravenous dose.

Specific Populations

Sex

No significant pharmacokinetic differences based on sex have been observed for AZSTARYS.

Race

There is insufficient experience with the use of AZSTARYS to detect ethnic variations in pharmacokinetics.

Age

The shapes of the plasma concentration time profiles for dexmethylphenidate were similar in pediatric patients (6 to 17 years of age) with ADHD and healthy adults. After the same dose administration of AZSTARYS, dexmethylphenidate exposure in pediatric patients (13 to 17 years of age) and adults was about half of that in pediatric patients 6 to 12 years of age. Plasma concentrations of dexmethylphenidate when adjusted for dose and body weight were similar across all age groups.

Renal Impairment

There is no experience with the use of AZSTARYS in patients with renal impairment. Since renal clearance is not an important route of serdexmethylphenidate or methylphenidate elimination, renal impairment is expected to have little effect on the pharmacokinetics of AZSTARYS.

Hepatic Impairment

There is no experience with the use of AZSTARYS in patients with hepatic impairment.

Drug Interaction Studies

Clinical Studies

CYP2D6 substrate: No clinically significant differences in desipramine (CYP2D6 substrate) were observed when co-administered with methylphenidate.

In Vitro Studies

Alcohol: No clinically significant differences in the rate or amount of release of either serdexmethylphenidate or methylphenidate were observed with alcohol concentrations of 5% and 40%.

Cytochrome P450 (CYP) enzymes: Serdexmethylphenidate and methylphenidate do not appear to be substrates, inducers or inhibitors of CYP1A2, 2C8, 2C9, 2C19, 2D6, 2E1 or 3A.

Transporters: Serdexmethylphenidate does not appear to be a substrate or inhibitor of P-gp, BCRP, OATP1B1/3, OAT1/3, OCT2, or MATE1/2-K.

13 NONCLINICAL TOXICOLOGY

13.1 Carcinogenesis, Mutagenesis, Impairment of Fertility

Carcinogenesis

Lifetime studies to evaluate the carcinogenic potential of serdexmethylphenidate have not been conducted.

Lifetime carcinogenicity studies have not been carried out with dexmethylphenidate hydrochloride.

In a lifetime carcinogenicity study carried out in B6C3F1 mice, racemic methylphenidate caused an increase in hepatocellular adenomas, and in males only, an increase in hepatoblastomas was seen at a daily dose of approximately 60 mg/kg/day. This dose is approximately 4 times the MRHD of 40 mg of dexmethylphenidate hydrochloride on a mg/m^2 basis. Hepatoblastoma is a relatively rare rodent malignant tumor type. There was no increase in total malignant hepatic tumors. The mouse strain used is sensitive to the development of hepatic tumors, and the significance of these results to humans is unknown.

Racemic methylphenidate hydrochloride did not cause any increase in tumors in a lifetime carcinogenicity study carried out in F344 rats; the highest dose used was approximately 45 mg/kg/day, which is approximately 5 times the MRHD of 40 mg of dexmethylphenidate hydrochloride on a mg/m^2 basis.

In a 24-week carcinogenicity study with racemic methylphenidate in the transgenic mouse strain p53+/-, which is sensitive to genotoxic carcinogens, there was no evidence of carcinogenicity. Male and female mice were fed diets containing the same concentrations as in the lifetime carcinogenicity study; the high-dose group was exposed to 60 to 74 mg/kg/day of racemic methylphenidate hydrochloride.

Mutagenesis

Serdexmethylphenidate was not mutagenic in the in vitro Ames reverse mutation assay, in the in vitro mammalian cell micronucleus assay using human peripheral blood lymphocytes, in the in vivo rat bone barrow micronucleus assay, or in the in vivo rat alkaline comet assay.

Dexmethylphenidate was not mutagenic in the in vitro Ames reverse mutation assay, in the in vitro mouse lymphoma cell forward mutation assay, or in the in vivo mouse bone marrow micronucleus test. In an in vitro assay using cultured Chinese Hamster Ovary (CHO) cells treated with racemic methylphenidate, sister chromatid exchanges and chromosome aberrations were increased, indicative of a weak clastogenic response.

Impairment of Fertility

Racemic methylphenidate hydrochloride did not impair fertility in male or female mice that were fed diets containing the drug in an 18-week continuous breeding study. The study was conducted at doses of up to 160 mg/kg/day, approximately 10-times the MRHD of 40 mg of dexmethylphenidate hydrochloride on a mg/m^2 basis.

14 CLINICAL STUDIES

Pediatric Patients 6 to 12 years of age with ADHD

The efficacy of AZSTARYS for the treatment of ADHD in pediatric patients 6 to 12 years of age was evaluated in a randomized, double-blind, placebo-controlled, parallel group, analog classroom study (Study 1; NCT# 03292952). That study was conducted in 150 pediatric patients 6 to 12 years of age who met Diagnostic and Statistical Manual of Mental Disorders, 5th edition (DSM-5) criteria for a primary diagnosis of ADHD (combined, inattentive, or hyperactive/impulsive presentation) confirmed by the Mini International Neuropsychiatric Interview for Children and Adolescents (MINI-KID).

Following washout of previous ADHD medication, subjects entered an open-label dose- optimization period (3 weeks) with an initial dosage of 39.2 mg/7.8 mg once daily in the morning. The dose could be titrated on a weekly basis to either 26.1 mg/5.2 mg, 39.2 mg/7.8 mg, or 52.3 mg/10.4 mg, until an optimal dose or the maximum dosage of 52.3 mg/10.4 mg/day was reached. At the end of optimization period, subjects were randomly assigned into a 1-week parallel group treatment period to receive either the individually optimized dose of AZSTARYS (mean dose of 45.6 mg/9.0 mg) or placebo.

At the end of the 1-week treatment period, raters evaluated the attention and behavior of the subjects in a laboratory classroom setting over a period of 13 hours using the Swanson, Kotkin, Agler, M-Flynn, and Pelham (SKAMP) rating scale. SKAMP is a validated 13-item teacher-rated scale that assesses manifestations of ADHD in a classroom setting. On this day, the dose was administered in the morning immediately after breakfast.

The primary efficacy endpoint was the mean change from baseline (pre-dose at randomization visit) of the SKAMP-Combined scores averaged across the test day (not including baseline score), with assessments conducted at 0.5, 1, 2, 4, 8, 10, 12, and 13 hours post-dose.

The mean change from baseline in the SKAMP-Combined scores, averaged across the test day, was statistically significantly lower (indicating improvement) with AZSTARYS compared to placebo (Table 2).

Table 2: Primary Efficacy Measure: SKAMP-Combined Scores Averaged Over Classroom Day in Pediatric Patients (6 to 12 years) with ADHD
Study Number | Treatment Group | N | Mean Baseline Score* (SD) | LS Mean Change from Baseline† (SE) | Placebo-subtracted Difference‡ (95% CI)
Study 1 | AZSTARYS (26.1 /5.2, 39.2/7.8, 52.3/10.4 mg/day) | 74 | 17.9 (9.2) | -4.87 (0.62) | -5.4 (-7.1, -3.7)
Study 1 | Placebo | 76 | 17.9 (10.4) | 0.54 (0.70) | -5.4 (-7.1, -3.7)
SD: standard deviation; SE: standard error; LS Mean: least-squares mean; CI: confidence interval.
* Baseline score assessed at pre-dose on the practice classroom day/randomization visit after 2 days of active drug washout.
† Classroom day least-squares mean change from baseline over hours 0.5. 1, 2, 4, 8, 10, 12, and 13.
‡ Difference (active drug minus placebo) in least-squares mean change from baseline.

Figure 2: LS Mean Change in SKAMP-Combined Score from Baseline after Treatment with AZSTARYS or Placebo during Classroom Day in Pediatric Patients (6 to 12 years) with ADHD

Adults and Pediatric Patients 13 to 17 years of age with ADHD

The efficacy of 52.3 mg/10.4 mg AZSTARYS in adults and pediatric patients 13 to 17 years of age was established by pharmacokinetic bridging between AZSTARYS (52.3 mg/10.4 mg) and dexmethylphenidate hydrochloride extended-release capsules [see Clinical Pharmacology (12.3)].

16 HOW SUPPLIED/STORAGE AND HANDLING

AZSTARYS (serdexmethylphenidate/dexmethylphenidate) capsules are available as follows:

- 26.1 mg/5.2 mg Capsules – blue cap/grey body, imprinted with "286" on cap and "KP415" on the body
  Bottles of 100 ................................................................... NDC 65038-0286-99
- 39.2 mg/7.8 mg Capsules – dark blue cap/grey body, imprinted with "429" on cap and "KP415" on the body
  Bottles of 100 ................................................................... NDC 65038-0429-99
- 52.3 mg/10.4 mg Capsules – orange cap/grey body, imprinted with "5612" on cap and "KP415" on the body
  Bottles of 100 ................................................................... NDC 65038-0561-99

Storage

Store at 20°C to 25°C (68°F to 77°F); excursions permitted between 15°C to 30°C (59°F to 86°F). [See USP Controlled Room Temperature]. Protect from moisture.

Dispense in tight container (USP).

17 PATIENT COUNSELING INFORMATION

Advise the patient to read the FDA-approved patient labeling (Medication Guide).

Abuse, Misuse, and Addiction

Educate patients and their families about the risks of abuse, misuse, and addiction of AZSTARYS, which can lead to overdose and death, and proper disposal of any unused drug [see Warnings and Precautions (5.1), Drug Abuse and Dependence (9.2), Overdosage (10)]. Advise patients to store AZSTARYS in a safe place, preferably locked, and instruct patients to not give AZSTARYS to anyone else.

Risk to Patients with Serious Cardiac Disease

Advise patients that there are potential risks to patients with serious cardiac disease, including sudden death, with AZSTARYS use. Instruct patients to contact a healthcare provider immediately if they develop symptoms such as exertional chest pain, unexplained syncope, or other symptoms suggestive of cardiac disease [see Warnings and Precautions (5.2)].

Increased Blood Pressure and Heart Rate

Advise patients and their caregivers that AZSTARYS can elevate blood pressure and heart rate [see Warnings and Precautions (5.3)].

Psychiatric Adverse Reactions

Advise patients and their caregivers that AZSTARYS, at recommended doses, can cause psychotic or manic symptoms, even in patients without a prior history or psychotic symptoms or mania [see Warnings and Precautions (5.4)].

Priapism

Advise patients and their caregivers of the possibility of painful or prolonged penile erections (priapism). Instruct the patient to seek immediate medical attention in the event of priapism [see Warnings and Precautions (5.5)].

Circulation Problems in Fingers and Toes [Peripheral vasculopathy, including Raynaud's phenomenon]

- Instruct patients about the risk of peripheral vasculopathy, including Raynaud's phenomenon, and associated signs and symptoms: fingers or toes may feel numb, cool, painful, and/or may change color from pale, to blue, to red.
- Instruct patients to report to their physician any new numbness, pain, skin color change, or sensitivity to temperature in fingers or toes.
- Instruct patients to call their physician immediately with any signs of unexplained wounds appearing on fingers or toes while taking AZSTARYS.
- Further clinical evaluation (e.g., rheumatology referral) may be appropriate for certain patients [see Warnings and Precautions (5.6)].

Long-Term Suppression of Growth in Pediatric Patients

Advise patients and their caregivers that AZSTARYS can cause slowing of growth and weight loss [see Warnings and Precautions (5.7)].

Increased Intraocular Pressure (IOP) and Glaucoma

Advise patients that IOP and glaucoma may occur during treatment with AZSTARYS [see Warnings and Precautions (5.9)].

Motor and Verbal Tics, and Worsening of Tourette’s Syndrome

Advise patients that motor and verbal tics and worsening of Tourette’s Syndrome may occur during treatment with AZSTARYS. Instruct patients to notify their healthcare provider if emergence of new tics or worsening of tics or Tourette’s syndrome occurs [see Warnings and Precautions (5.10)].

Administration Instructions

Advise patients and their caregivers to administer AZSTARYS capsules whole or opened and sprinkled over applesauce or added to water. If sprinkled, advise patients and their caregivers to consume all the drug/food mixture immediately or within 10 minutes of mixing and not to store for future use [see Dosage and Administration (2.3)].

Pregnancy Registry

Advise patients that there is a pregnancy exposure registry that monitors pregnancy outcomes in females exposed to AZSTARYS during pregnancy [see Use in Specific Populations (8.1)].

Lactation

Advise nursing mother to monitor infants exposed to AZSTARYS through breastmilk for agitation, poor feeding, and reduced weight gain [see Use in Specific Populations (8.2)].

Distributed by:
Corium, LLC
55 Cambridge Parkway, Suite 401
Cambridge, MA 02142

Medication Guide
AZSTARYS® (az star’ is)
(serdexmethylphenidate and dexmethylphenidate) capsules, CII

What is the most important information I should know about AZSTARYS?

AZSTARYS can cause serious side effects, including:

- Abuse misuse, and addiction. AZSTARYS has a high chance for abuse and misuse and may lead to substance use problems, including addiction. Misuse and abuse of AZSTARYS, other methylphenidate containing medicines, and amphetamine containing medicines, can lead to overdose and death. The risk of overdose and death is increased with higher doses of AZSTARYS or when it is used in ways that are not approved, such as snorting or injection.
- Your healthcare provider should check you or your child’s risk for abuse, misuse, and addiction before starting treatment with AZSTARYS and will monitor you or your child during treatment.
- AZSTARYS may lead to physical dependence after prolonged use, even if taken as directed by your healthcare provider.
- Do not give AZSTARYS to anyone else. See “What is AZSTARYS?” for more information.
- Keep AZSTARYS in a safe place and properly dispose of any unused medicine. See “How should I store AZSTARYS?”for more information.
  - Tell your healthcare provider if you or your child have ever abused or been dependent on alcohol, prescription medicines, or street drugs.
- Risks for people with serious heart disease. Sudden death has happened in people who have heart defects or other serious heart disease.
  Your healthcare provider should check you or your child carefully for heart problems before starting treatment with AZSTARYS. Tell your healthcare provider if you or your child have any heart problems, heart disease, or heart defects.
  Call your healthcare provider or go to the nearest hospital emergency room right away if you or your child have any signs of heart problems such as chest pain, shortness of breath, or fainting during treatment with AZSTARYS.

- Increased blood pressure and heart rate.

Your healthcare provider should check you or your child’s blood pressure and heart rate regularly during treatment with AZSTARYS.

- Mental (psychiatric) problems, including:
  - new or worse behavior and thought problems
  - new or worse bipolar illness
  - new psychotic symptoms (such as hearing voices, or seeing or believing things that are not real) or new manic symptoms
    Tell your healthcare provider about any mental problems you or your child have, or about a family history of suicide, bipolar illness, or depression.
    Call your healthcare provider right away if you or your child have any new or worsening mental symptoms or problems during treatment with AZSTARYS, especially hearing voices, seeing or believing things that are not real, or new manic symptoms.

What is AZSTARYS?

AZSTARYS is a central nervous system stimulant prescription medicine used for the treatment of Attention-Deficit Hyperactivity Disorder (ADHD) in people 6 years of age and older. AZSTARYS may help increase attention and decrease impulsiveness and hyperactivity in people 6 years of age and older with ADHD.

AZSTARYS is not recommended for use in children under 6 years of age with ADHD.

AZSTARYS is a federally controlled substance (CII) because it contains dexmethylphenidate that can be a target for people who abuse prescription medicines or street drugs. Keep AZSTARYS in a safe place to protect it from theft. Never give AZSTARYS to anyone else because it may cause death or harm them. Selling or giving away AZSTARYS may harm others and is against the law.

Do not take AZSTARYS if you or your child are:

- allergic to serdexmethylphenidate, methylphenidate, or any of the ingredients in AZSTARYS. See the end of this Medication Guide for a complete list of ingredients in AZSTARYS.
- taking or have stopped taking within the past 14 days a medicine used to treat depression called a monoamine oxidase inhibitor (MAOI).

Before taking AZSTARYS, tell your healthcare provider about all medical conditions, including if you or your child:

- have heart problems, heart disease, heart defects, or high blood pressure
- have mental problems including psychosis, mania, bipolar illness, or depression, or has a family history of suicide, bipolar illness, or depression
- have circulation problems in fingers and toes
- have eye problems, including increased pressure in your eye, glaucoma, or problems with your close-up vision (farsightedness)
- have or had repeated movements or sounds (tics) or Tourrette's syndrome, or have a family history of tics or Tourette's syndrome
- are pregnant or plans to become pregnant. It is not known if AZSTARYS will harm the unborn baby.
  - There is a pregnancy registry for females who are exposed to ADHD medications, including AZSTARYS, during pregnancy. The purpose of the registry is to collect information about the health of females exposed to AZSTARYS and their baby. If you or your child becomes pregnant during treatment with AZSTARYS, talk to your healthcare provider about registering with the National Pregnancy Registry for Psychostimulants at 1-866-961-2388.
- are breastfeeding or plans to breastfeed. AZSTARYS passes into breast milk. Talk to your healthcare provider about the best way to feed the baby during treatment with AZSTARYS.

Tell your healthcare provider about all of the medicines that you or your child take, including prescription and over-the-counter medicines, vitamins, and herbal supplements.

AZSTARYS and some medicines may interact with each other and cause serious side effects. Sometimes the doses of other medicines will need to be adjusted during treatment with AZSTARYS. Your healthcare provider will decide whether AZSTARYS can be taken with other medicines.

Especially tell your healthcare provider if you or your child takes: blood pressure medicines (anti-hypertensive)

Know the medicines that you or your child take. Keep a list of the medicines with you to show your healthcare provider and pharmacist. Do not start any new medicine during treatment with AZSTARYS without talking to your healthcare provider first.

How should AZSTARYS be taken?

- Take AZSTARYS exactly as prescribed.
- Your healthcare provider may change the dose if needed.
- Take AZSTARYS 1 time each day in the morning with or without food.
- AZSTARYS capsules may be swallowed whole with water or other liquids.
- If AZSTARYS capsules cannot be swallowed whole, the capsule may be opened and the entire contents sprinkled onto 2 tablespoonfuls of applesauce or into 2oz (50mL) of water.
  - Swallow all the applesauce or water mixture right away or within 10 minutes of mixing. Do not store applesauce or water and medicine mixture.

If you or your child take too much AZSTARYS, call your healthcare provider or Poison Help line at 1-800-222-1222 or go to the nearest hospital emergency room right away.

What are possible side effects of AZSTARYS?

AZSTARYS can cause serious side effects, including:

- See "What is the most important information I should know about AZSTARYS?"
- Painful and prolonged erections (priapism). Priapism has happened in males who take products that contain methylphenidate. If you or your child develops priapism, get medical help right away.
- Circulation problems in fingers and toes (peripheral vasculopathy, including Raynaud's phenomenon). Signs and symptoms may include:
  - fingers or toes may feel numb, cool, or painful
  - fingers or toes may change color from pale, to blue, to red
  Tell your healthcare provider if you or your child have numbness, pain, skin color change, or sensitivity to temperature in the fingers or toes.
  Call your healthcare provider right away if you or your child have any signs of unexplained wounds appearing on fingers or toes during treatment with AZSTARYS.
- Slowing of growth (height and weight) in children. Children should have their height and weight checked often during treatment AZSTARYS. AZSTARYS treatment may be stopped if your child is not growing or gaining weight.
- Eye problems (increased pressure in the eye and glaucoma). Call your healthcare provider right away if you or your child develop changes in your vision or eye pain, swelling, or redness.
- New or worsening tics or worsening Tourette’s syndrome. Tell your healthcare provider if you or your child get any new or worsening tics or worsening Tourette’s syndrome during treatment with AZSTARYS.

The most common side effects of AZSTARYS include:

- decreased appetite
- nausea
- indigestion
- weight loss
- dizziness
- mood swings
- increased blood pressure

- trouble sleeping
- vomiting
- stomach pain
- anxiety
- irritability
- increased heart rate

These are not all the possible side effects of AZSTARYS.

Call your doctor for medical advice about side effects. You may report side effects to FDA at 1-800-FDA-1088.

How should I store AZSTARYS?

- Store AZSTARYS in a safe place and in a tightly closed container at room temperature between at room temperature between 68°F to 77°F (20°C to 25°C).
- Dispose of remaining, unused, or expired AZSTARYS by a medicine take-back program at a U.S. Drug Enforcement Administration (DEA) authorized collection site. If no take-back program or authorized collector is available, mix AZSTARYS with an undesirable, nontoxic substance such as dirt, cat litter, or used coffee grounds to make it less appealing to children and pets. Place the mixture in a container such as a sealed plastic bag and throw away (discard) AZSTARYS in the household trash. Visit www.fda.gov/drugdisposal for additional information on disposal of unused medicines.

Keep AZSTARYS and all medicines out of the reach of children.

General information about the safe and effective use of AZSTARYS.

Medicines are sometimes prescribed for purposes other than those listed in a Medication Guide. Do not use AZSTARYS for a condition for which it was not prescribed. Do not give AZSTARYS to other people, even if they have the same symptoms that you have. It may harm them, and it is against the law. You can ask your healthcare provider or pharmacist for information about AZSTARYS that was written for healthcare professionals.

What are the ingredients in AZSTARYS?

Active ingredients: serdexmethylphenidate and dexmethylphenidate

Inactive ingredients: colloidal silicon dioxide, crospovidone, hypromellose, magnesium stearate, microcrystalline cellulose, talc, black iron oxide, titanium dioxide, FD&C Blue No. 1 (26/5.2 mg and 39/7.8 mg), FD&C Red No. 40 (39/7.8 mg and 52/10.4 mg), FD&C Yellow No. 6 (52/10.4 mg)

Distributed by Corium, LLC, 55 Cambridge Parkway, Suite 401, Cambridge, MA 02142

For more information call 1-855-253-2407 or go to www.AZSTARYS.com

This Medication Guide has been approved by the U.S. Food and Drug Administration.

Revised: 09/2025

REF-02399 09/2025